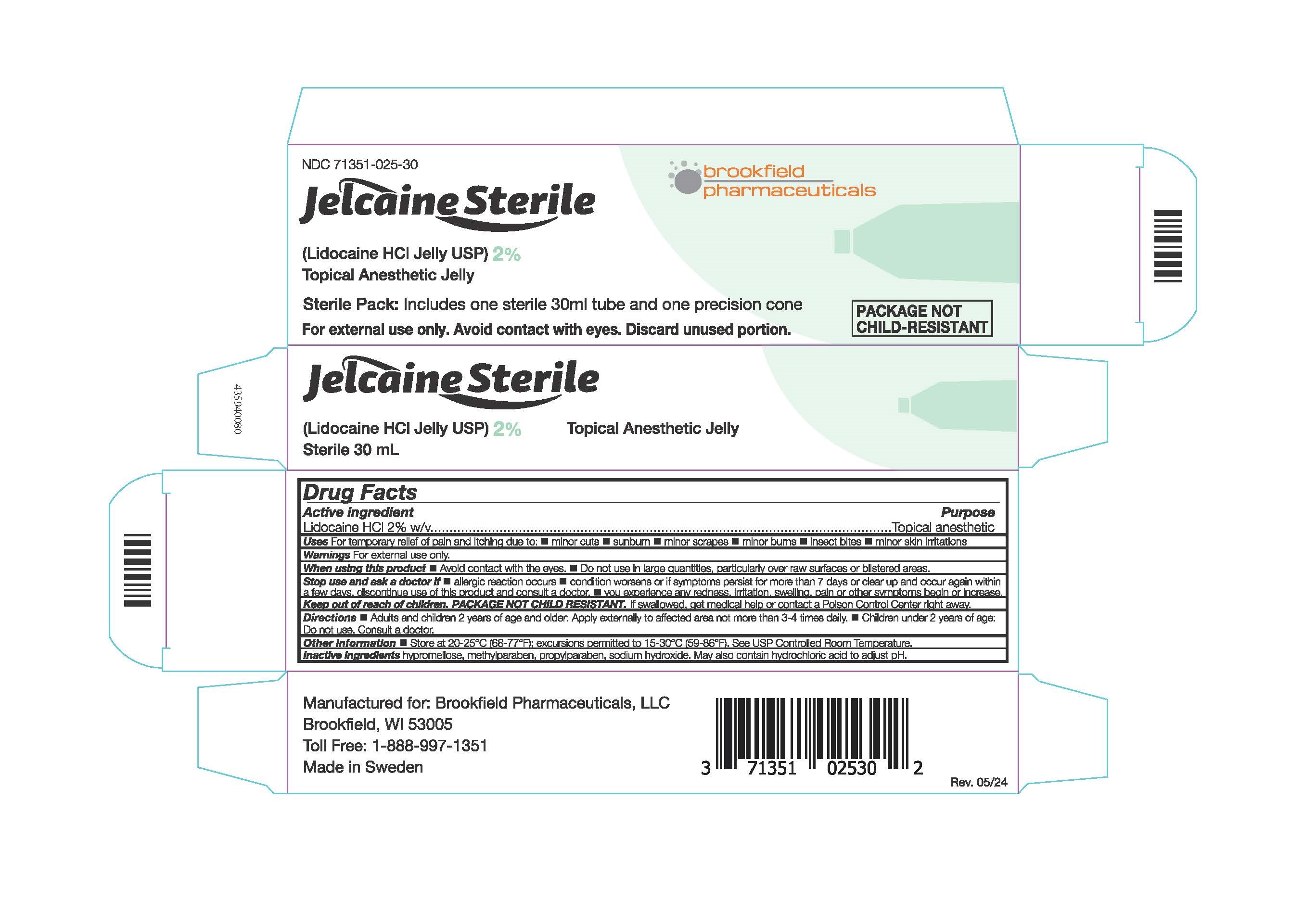 DRUG LABEL: Jelcaine Sterile
NDC: 71351-025 | Form: JELLY
Manufacturer: Brookfield Pharmaceuticals, LLC
Category: otc | Type: HUMAN OTC DRUG LABEL
Date: 20251110

ACTIVE INGREDIENTS: LIDOCAINE HYDROCHLORIDE 20 mg/1 mL
INACTIVE INGREDIENTS: HYDROCHLORIC ACID; METHYLPARABEN; PROPYLPARABEN; SODIUM HYDROXIDE; HYPROMELLOSES

Jelcaine Sterile

Active Ingredients

Lidocaine HCl 2% w/v

Purpose

Topical anesthetic

Uses

For temporary relief of pain and itching due to:

- minor cuts
- sunburn
- minor scrapes
- minor burns
- insect bites
- minor skin irritations

Warnings

For external use only.

When using this product

- Avoid contact with eyes.
- Do not use in large quantities, particularly over raw surfaces or blistered areas.

Stop use and ask a doctor if

- allergic reaction occurs
- condition worsens or if symptoms persist for more than 7 days or clear up and occur again within a few days, discontinue use of this product and consult a doctor
- you experience any redness, irritation, swelling, pain or other symptoms begin or increase

Keep out of reach of children

PACKAGE NOT CHILD RESISTANT. If swallowed, get medical help or contact a Poison Control Center right away.

Directions

- Adults and children 2 years of age and older: Apply externally to the affected area not more than 3-4 time daily.
- Children under 2 years of age: Do not use. Consult a doctor.

Other information

- Store at 20-25°C (68-77°F); excursions permitted to 15-30°C (59-86°F). See USP Controlled Room Temperature.

Inactive ingredients

hypromellose, methylparaben, propylparaben, sodium hydroxide. May also contain hydrochloric acid to adjust pH.